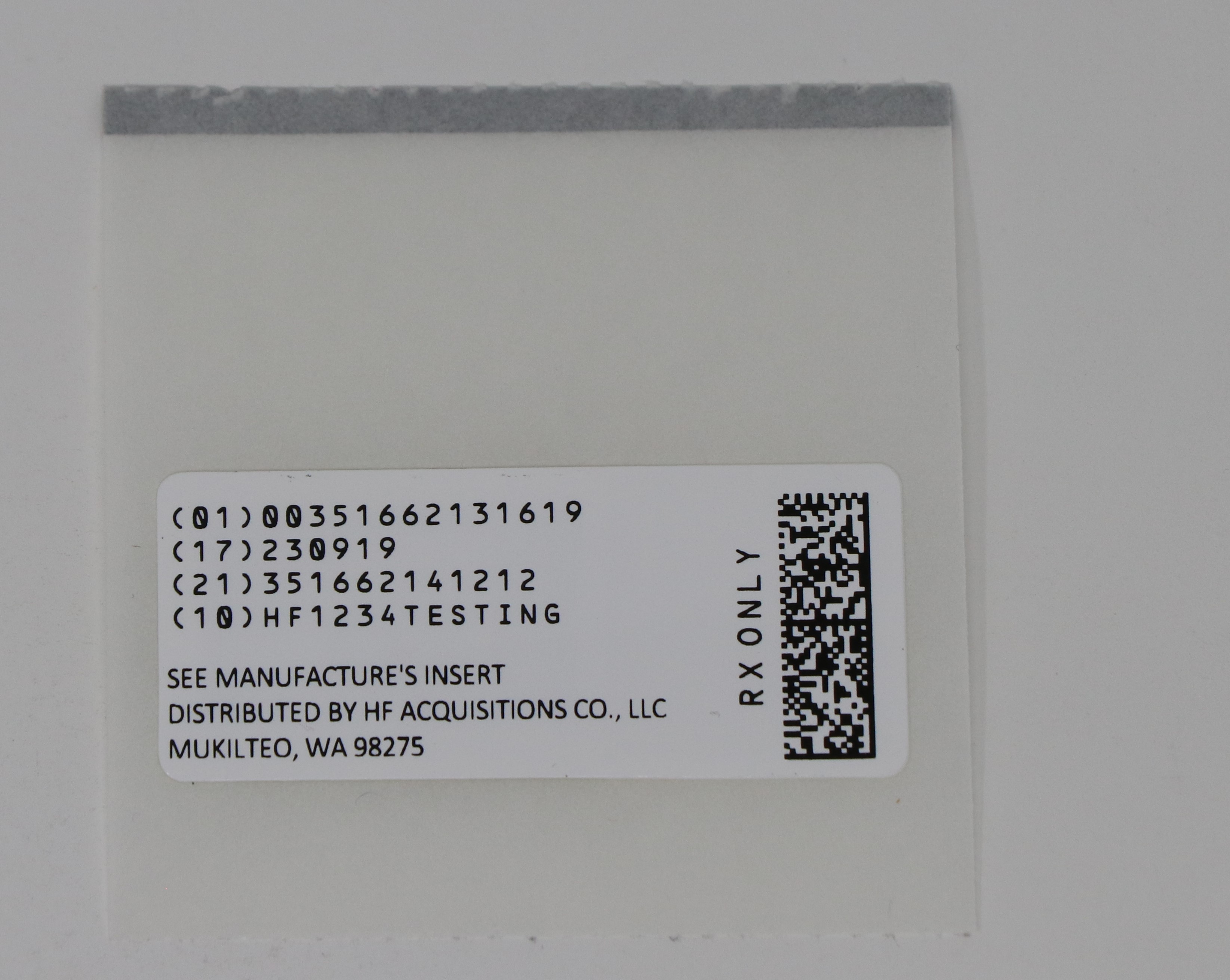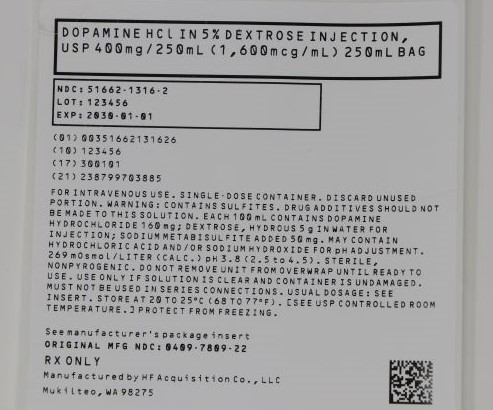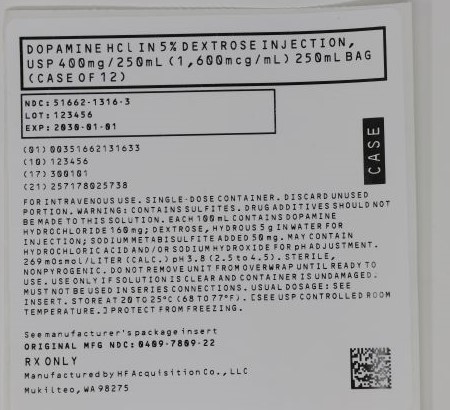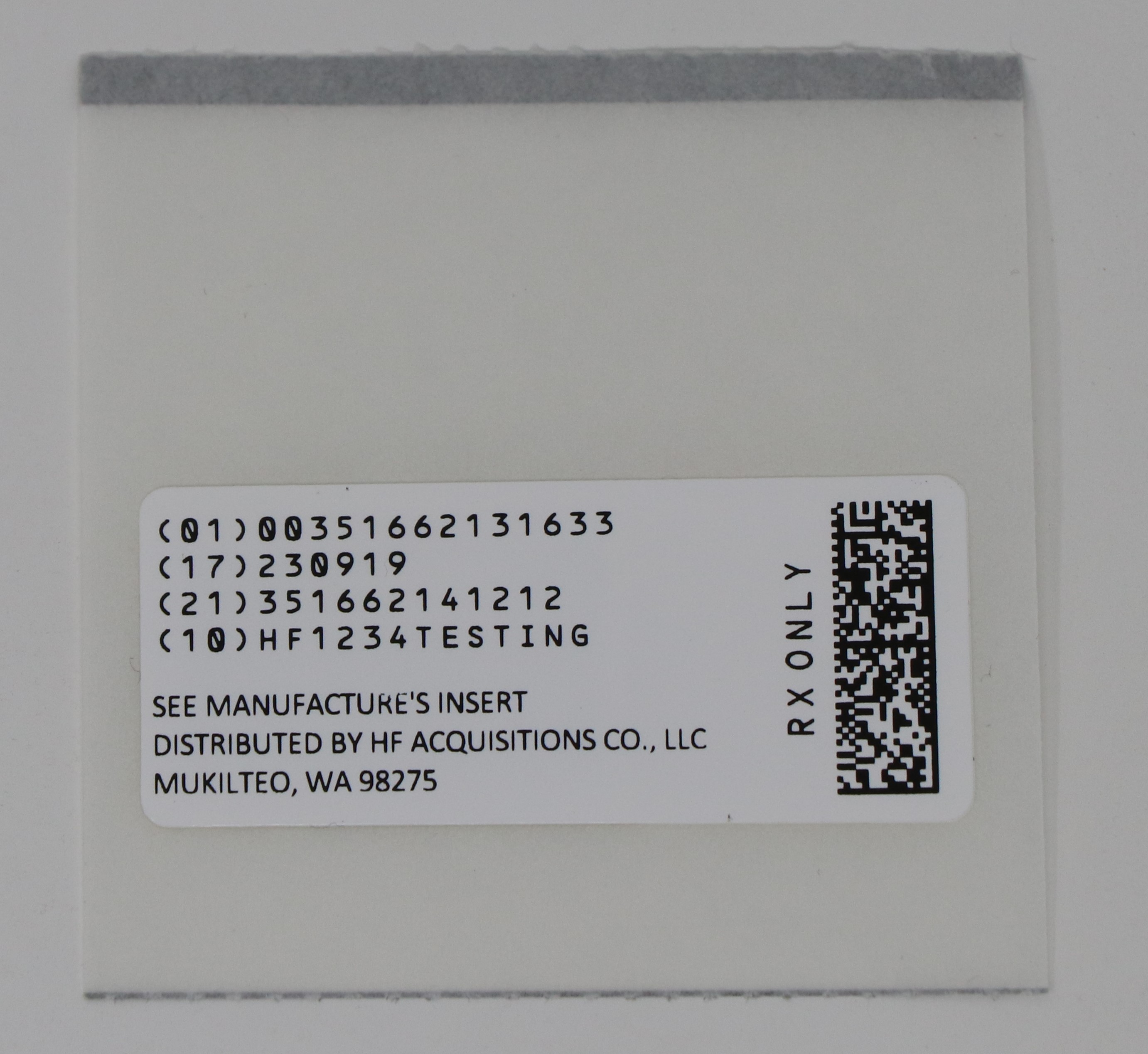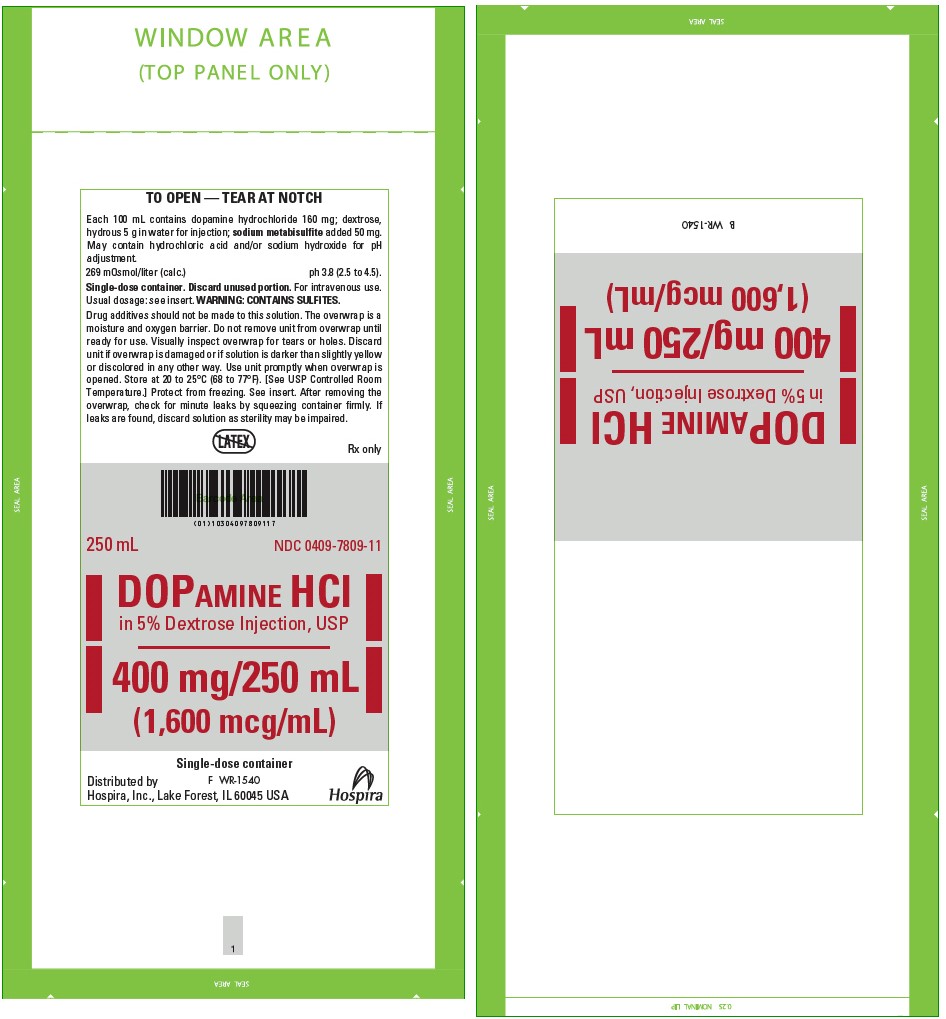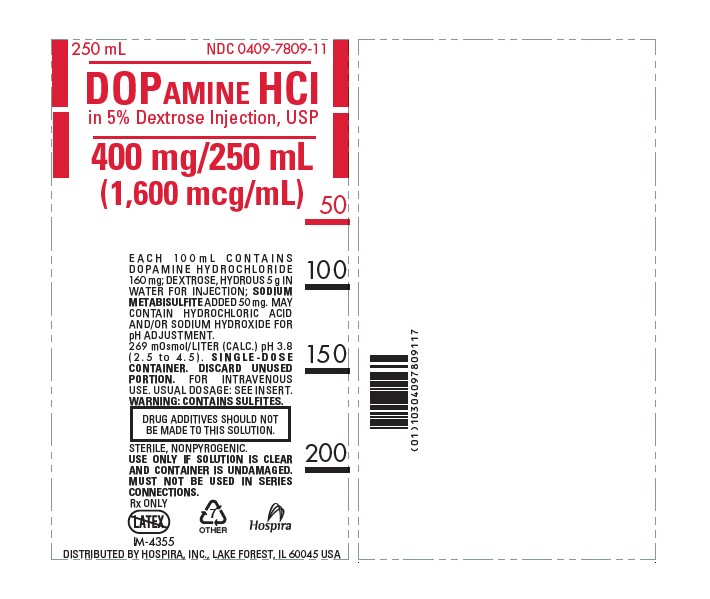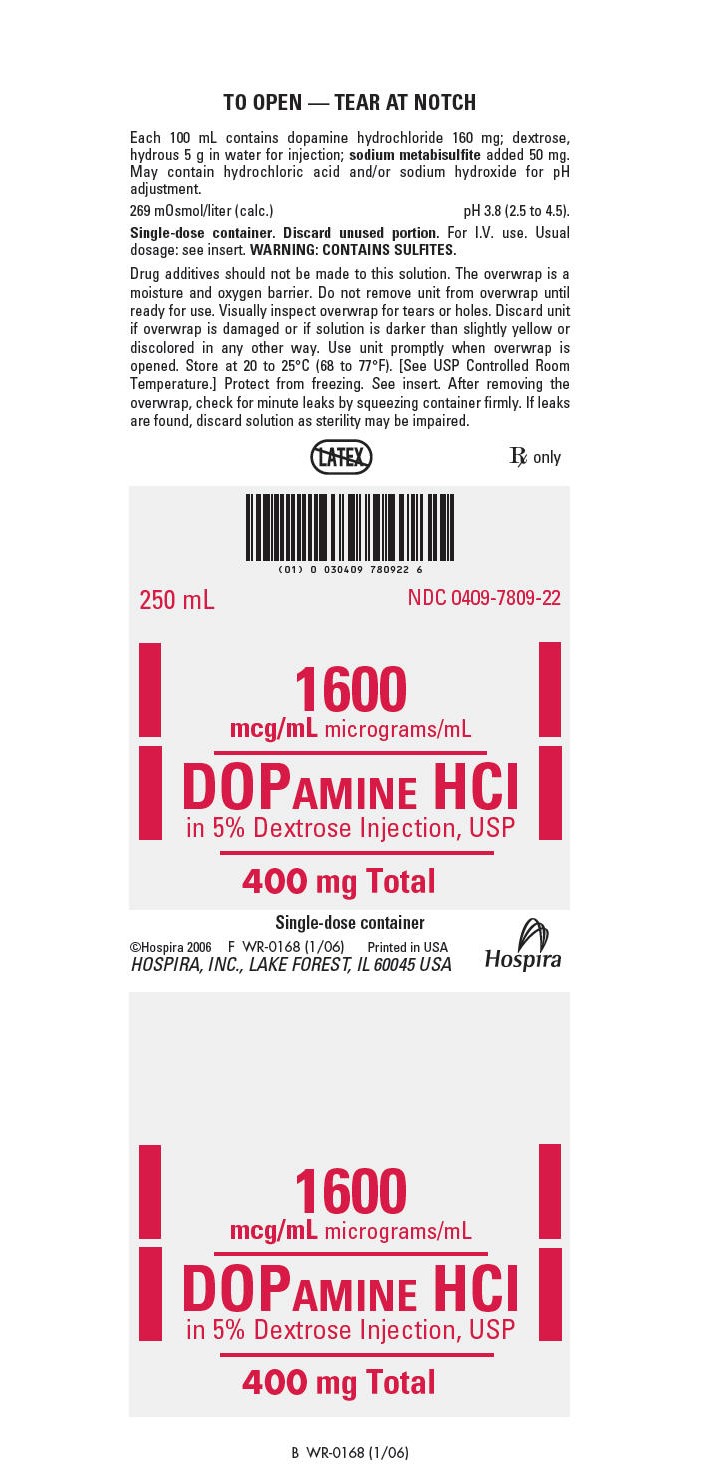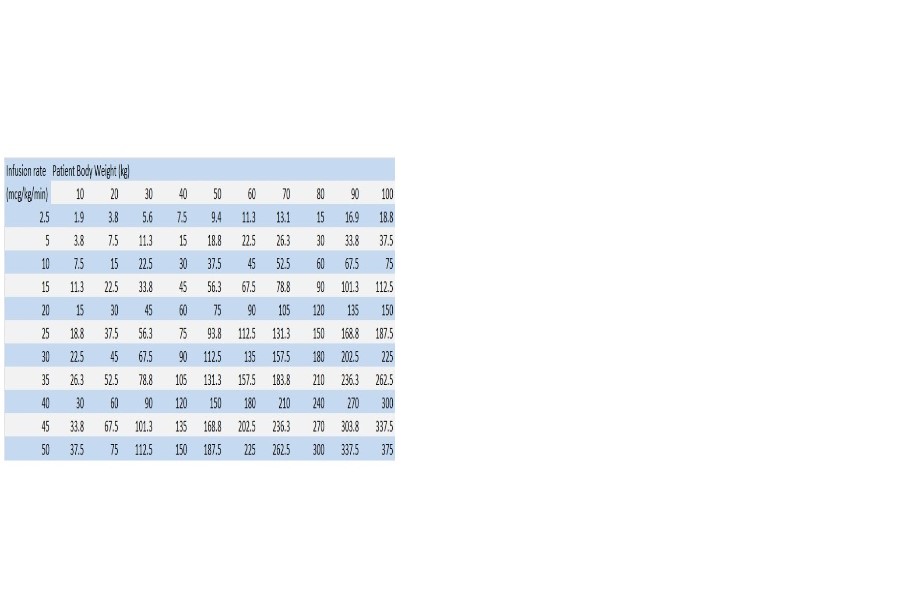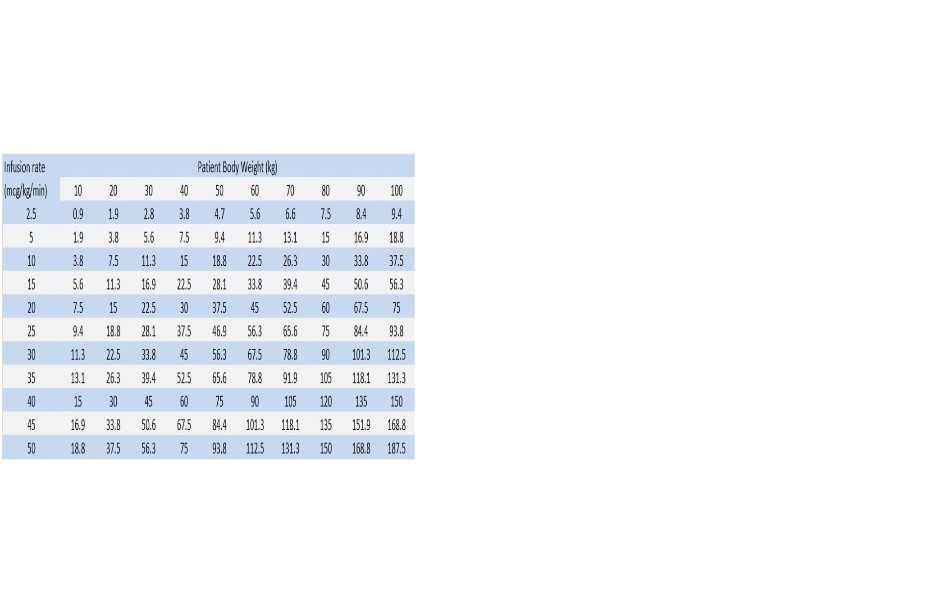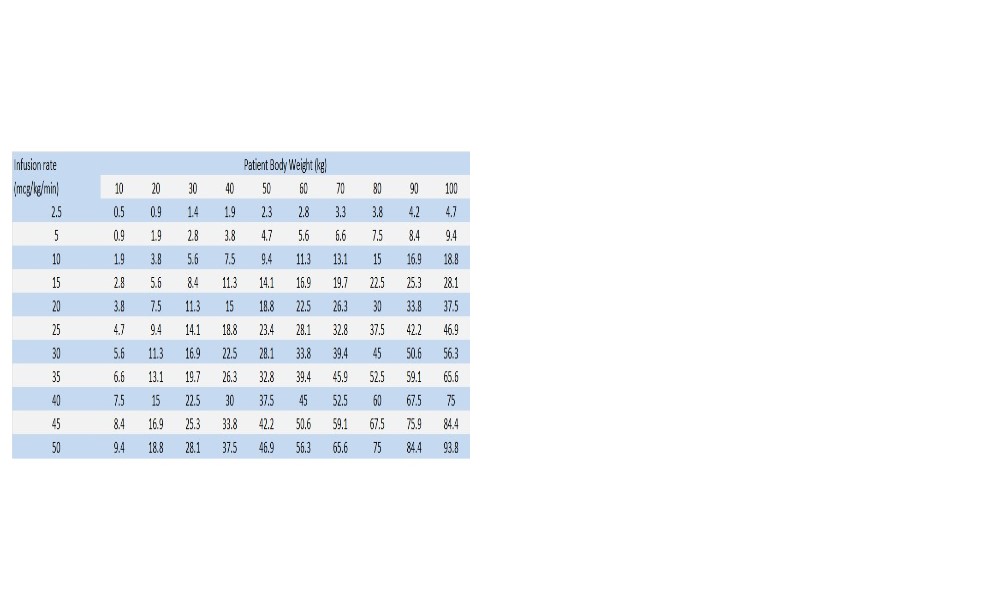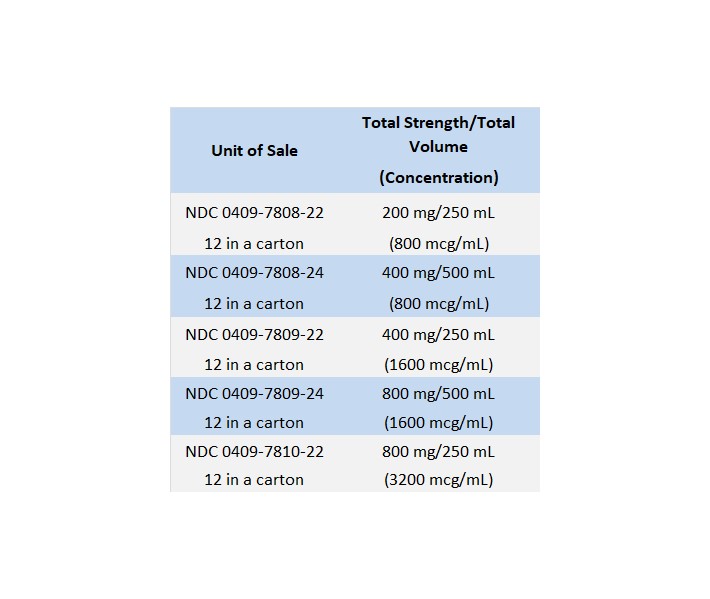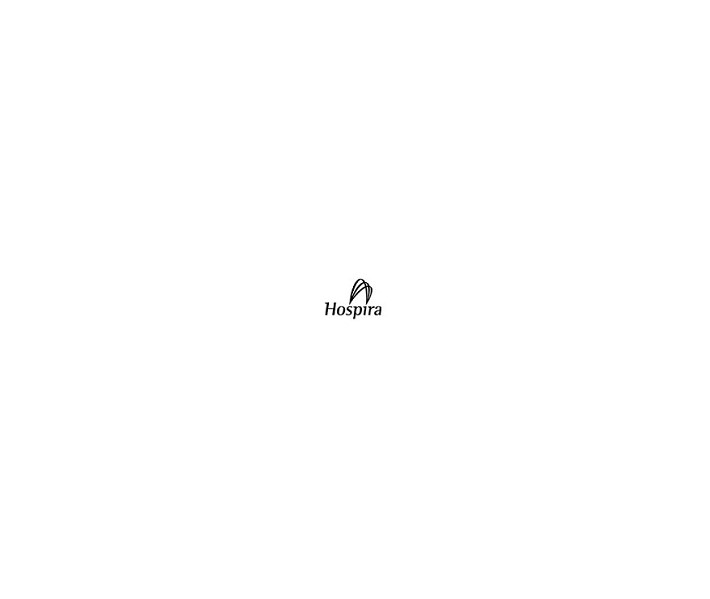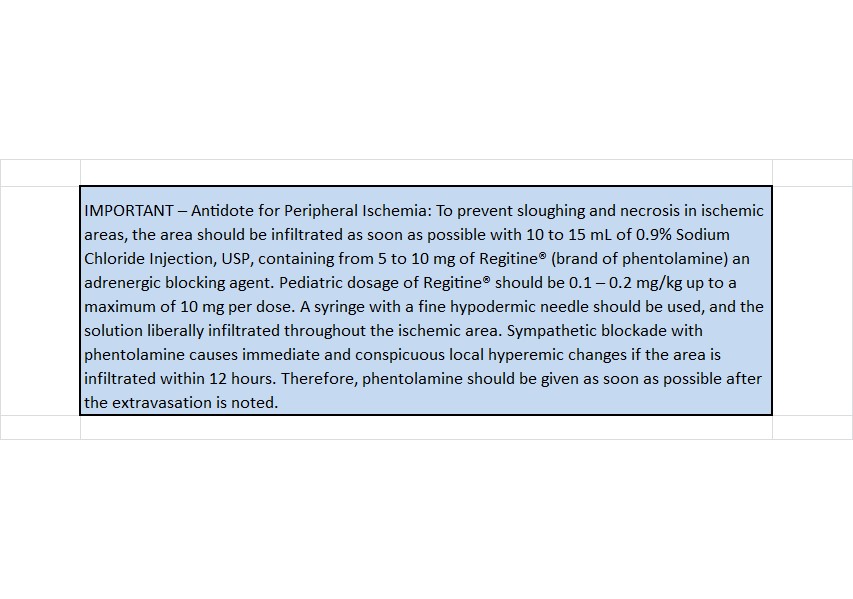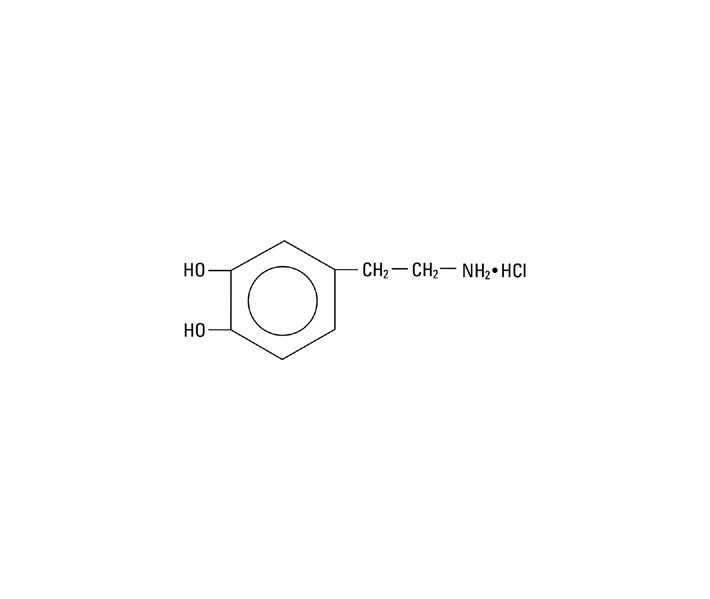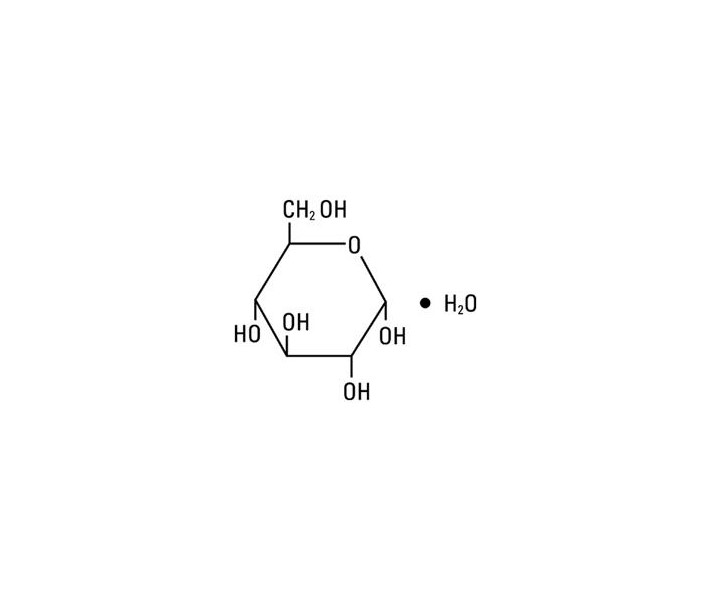 DRUG LABEL: DOPAMINE HYDROCHLORIDE
NDC: 51662-1316 | Form: INJECTION, SOLUTION
Manufacturer: HF Acquisition Co LLC, DBA HealthFirst
Category: prescription | Type: HUMAN PRESCRIPTION DRUG LABEL
Date: 20240129

ACTIVE INGREDIENTS: DOPAMINE HYDROCHLORIDE 1.6 mg/1 mL
INACTIVE INGREDIENTS: WATER; SODIUM HYDROXIDE; DEXTROSE MONOHYDRATE; SODIUM METABISULFITE; HYDROCHLORIC ACID

DOPAMINE HYDROCHLORIDE IN 5% DEXTROSE INJECTION, USP 400mg 250mL BAG

SPL UNCLASSIFIED

Aqueous Solutions for Acute Correction of Hemodynamics in Shock States

Flexible Plastic Container

DESCRIPTION

Dopamine Hydrochloride in 5% Dextrose Injection, USP is a sterile, nonpyrogenic, prediluted solution of dopamine hydrochloride in 5% dextrose injection. It is administered by intravenous infusion.

Each 100 mL contains dopamine hydrochloride 80 mg (0.8 mg/mL), 160 mg (1.6 mg/mL) or 320 mg (3.2 mg/mL) and dextrose, hydrous 5 g in water for injection, with sodium metabisulfite added 50 mg as a stabilizer; osmolar concentration, respectively 261, 269, or 286 mOsmol/liter (calc.), pH 3.8 (2.5 to 4.5). May contain hydrochloric acid and/or sodium hydroxide for pH adjustment.

Dopamine administered intravenously is a myocardial inotropic agent, which also may increase mesenteric and renal blood flow plus urinary output.

Dopamine Hydrochloride is chemically designated 3, 4-dihydroxyphenethylamine hydrochloride (C8H11NO2 • HCl), a white crystalline powder freely soluble in water. It has the following structural formula:

Dopamine (also referred to as 3-hydroxytyramine) is a naturally occurring endogenous catecholamine precursor of norepinephrine.

Dextrose, USP is chemically designated D-glucose monohydrate (C6H12O6 • H2O), a hexose sugar freely soluble in water. It has the following structural formula:

Water for Injection, USP is chemically designated H2O.

The flexible plastic container is fabricated from a specially formulated CR3 plastic material. Water can permeate from inside the container into the overwrap but not in amounts sufficient to affect the solution significantly. Solutions in contact with the plastic container may leach out certain chemical components from the plastic in very small amounts; however, biological testing was supportive of the safety of the plastic container materials. Exposure to temperatures above 25°C/77°F during transport and storage will lead to minor losses in moisture content. Higher temperatures lead to greater losses. It is unlikely that these minor losses will lead to clinically significant changes within the expiration period.

CLINICAL PHARMACOLOGY

Dopamine exhibits an inotropic action on the myocardium, resulting in increased cardiac output. It causes less increase in myocardial oxygen consumption than isoproterenol and the effect of dopamine usually is not associated with tachyarrhythmia. Reported clinical studies have revealed that the drug usually increases systolic and pulse pressure without any or only a minor elevating effect on diastolic pressure. Total peripheral resistance at low and intermediate doses is usually unchanged. Blood flow to peripheral vascular beds may decrease while mesenteric blood flow is increased. The drug also has been reported to produce dilation of the renal vasculature which is accompanied by increases in glomerular filtration rate, renal blood flow and sodium excretion. Increased urinary output produced by dopamine is usually not associated with decreased urine osmolality.

Solutions containing carbohydrate in the form of dextrose restore blood glucose levels and provide calories. Carbohydrate in the form of dextrose may aid in minimizing liver glycogen depletion and exerts a protein-sparing action. Dextrose injected parenterally undergoes oxidation to carbon dioxide and water.

Water is an essential constituent of all body tissues and accounts for approximately 70% of total body weight. Average normal adult daily requirement ranges from two to three liters (1.0 to 1.5 liters each for insensible water loss due to perspiration and urine production).

Water balance is maintained by various regulatory mechanisms. Water distribution depends primarily on the concentration of electrolytes and sodium (Na+) plays a major role in maintaining physiologic equilibrium.

The reported clearance rate of dopamine in critically ill infants and children has ranged from 46 to 168 mL/kg/min, with the higher values seen in the younger patients. The apparent volume of distribution in neonates is reported as 0.6 to 4 L/kg, leading to an elimination half-life of 5 to 11 minutes.

INDICATIONS & USAGE

Dopamine Hydrochloride in 5% Dextrose Injection, USP is indicated for the correction of hemodynamic imbalances present in shock due to myocardial infarction, trauma, endotoxic septicemia, open heart surgery, renal failure and chronic cardiac decompensation as in refractory congestive failure.

When indicated, restoration of circulatory volume should be instituted or completed with a suitable plasma expander or whole blood, prior to administration of dopamine hydrochloride.

Patients most likely to respond to dopamine are those whose physiological parameters (such as urine flow, myocardial function and blood pressure) have not undergone extreme deterioration. Reports indicate that the shorter the time between onset of signs and symptoms and initiation of therapy with volume restoration and dopamine, the better the prognosis.

Poor Perfusion of Vital Organs: Although urine flow is apparently one of the better diagnostic signs for monitoring vital organ perfusion, the physician also should observe the patient for signs of reversal of mental confusion or coma. Loss of pallor, increase in toe temperature or adequacy of nail bed capillary filling also may be observed as indices of adequate dosage. Reported studies indicate that when dopamine is administered before urine flow has decreased to approximately 0.3 mL/minute prognosis is more favorable.

However, it has been observed that in some oliguric or anuric patients, administration of the drug has produced an increase in urine flow which may reach normal levels. The drug also may increase urine flow in patients whose output is within normal limits and thus may help in reducing the degree of pre-existing fluid accumulation. Conversely, at higher than optimal doses for a given patient, urinary flow may decrease, requiring a reduction of dosage. Concomitant administration of dopamine and diuretic agents may produce an additive or potentiating effect.

Low Cardiac Output: Dopamine's direct inotropic effect on the myocardium which increases cardiac output at low or moderate doses is related to a favorable prognosis. Increased output has been associated with unchanged or decreased systemic vascular resistance (SVR). The association of static or decreased SVR with low or moderate increases in cardiac output is regarded as a reflection of differential effects on specific vascular beds, with increased resistance in peripheral beds (e.g., femoral), and concurrent decreases in mesenteric and renal vascular beds. Redistribution of blood flow parallels these changes so that an increase in cardiac output is accompanied by an increase in mesenteric and renal blood flow. In many instances the renal fraction of the total cardiac output has been found to increase. Increase in cardiac output produced by dopamine is not associated with substantial decreases in systemic vascular resistance as may occur with isoproterenol.

Hypotension: Low to moderate doses of dopamine, which have little effect on SVR, can be used to manage hypotension due to inadequate cardiac output. At high therapeutic doses, dopamine's α-adrenergic action becomes more prominent and thus may correct hypotension due to diminished SVR. As in other circulatory decompensation states, prognosis is better in patients whose blood pressure and urine flow have not undergone extreme deterioration. Therefore, it is suggested the physician administer dopamine as soon as a definite trend toward decreased systolic and diastolic pressure becomes apparent.

CONTRAINDICATIONS

Dopamine hydrochloride should not be used in patients with pheochromocytoma.

Dopamine should not be administered in the presence of uncorrected tachyarrhythmias or ventricular fibrillation.

WARNINGS

Do NOT add any alkalinizing substance, since dopamine is inactivated in alkaline solution.

Patients who have been treated with monoamine oxidase (MAO) inhibitors prior to administration of dopamine should receive substantially reduced dosage of the latter. See PRECAUTIONS, Drug Interactions, below.

Additive medications should not be delivered via this solution.

Dopamine Hydrochloride in 5% Dextrose Injection, USP contains sodium metabisulfite, a sulfite that may cause allergic-type reactions including anaphylactic symptoms and life-threatening or less severe asthmatic episodes in certain susceptible people. The overall prevalence of sulfite sensitivity in the general population is unknown and probably low. Sulfite sensitivity is seen more frequently in asthmatic than in nonasthmatic people.

PRECAUTIONS

General:

Solutions containing dextrose should be used with caution in patients with known subclinical or overt diabetes mellitus.

Fluid and Electrolyte Balance: Excess administration of potassium-free solutions may result in significant hypokalemia.

The intravenous administration of these solutions can cause fluid and/or solute overloading resulting in dilution of serum electrolyte concentrations, overhydration, congested states or pulmonary edema.

Careful Monitoring Required: Close monitoring of the following indices ─ urine flow, cardiac output and blood pressure ─ during dopamine infusion is necessary as in the case of any adrenergic agent.

Hypoxia, Hypercapnia, Acidosis: These conditions, which may also reduce the effectiveness and/or increase the incidence of adverse effects of dopamine, must be identified and corrected prior to, or concurrently with, administration of dopamine HCl.

Ventricular Arrhythmias: If an increased number of ectopic beats are observed the dose should be reduced if possible.

Hypotension: At lower infusion rates, if hypotension occurs, the infusion rate should be rapidly increased until adequate blood pressure is obtained. If hypotension persists, dopamine HCl should be discontinued and a more potent vasoconstrictor agent such as norepinephrine should be administered.

Occlusive Vascular Disease: Patients with a history of occlusive vascular disease (e.g., arteriosclerosis, arterial embolism, Raynaud's disease, cold injury such as frostbite, diabetic endarteritis, and Buerger's disease) should be closely monitored for any changes in color or temperature of the skin of the extremities. If a change in skin color or temperature occurs and is thought to be the result of compromised circulation to the extremities, the benefits of continued dopamine infusion should be weighed against the risk of possible necrosis. These changes may be reversed by decreasing the rate or discontinuing the infusion entirely.

Extravasation: Dopamine Hydrochloride in 5% Dextrose Injection, USP should be infused into a large vein whenever possible to prevent the possibility of infiltration of perivascular tissue adjacent to the infusion site. Extravasation may cause necrosis and sloughing of surrounding tissue. Large veins of the antecubital fossa are preferred to veins of the dorsum of the hand or ankle. Administration into an umbilical arterial catheter is not recommended. Less suitable infusion sites should be used only when larger veins are unavailable and the patient's condition requires immediate attention. The physician should switch to a more suitable site as soon as possible and the infusion site in use should be continuously monitored for free flow.

Laboratory Tests: Infusion of dopamine suppresses pituitary secretion of thyroid–stimulating hormone, growth hormone, and prolactin.

Weaning: When discontinuing the infusion, it may be necessary to gradually decrease the dose of dopamine HCl while expanding blood volume with intravenous fluids. Sudden cessation may result in marked hypotension.

Drug Interactions: Cyclopropane or halogenated hydrocarbon anesthetics increase cardiac autonomic irritability and may sensitize the myocardium to the action of certain intravenously administered catecholamines, such as dopamine. This interaction appears to be related both to pressor activity and to the β-adrenergic stimulating properties of these catecholamines, and may produce ventricular arrhythmias and hypertension. Therefore, EXTREME CAUTION should be exercised when administering dopamine HCl to patients receiving cyclopropane or halogenated hydrocarbon anesthetics. Results of studies in animals indicate that dopamine-induced ventricular arrhythmias during anesthesia can be reversed by propranolol.

Because dopamine is metabolized by monoamine oxidase (MAO), inhibition of this enzyme prolongs and potentiates the effect of dopamine. Patients who have been treated with MAO inhibitors within two to three weeks prior to the administration of dopamine should receive initial doses of dopamine hydrochloride no greater than one-tenth (1/10) of the usual dose.

Concurrent administration of low-dose dopamine HCl and diuretic agents may produce an additive or potentiating effect on urine flow.

Tricyclic antidepressants may potentiate the cardiovascular effects of adrenergic agents.

Cardiac effects of dopamine are antagonized by β-adrenergic blocking agents, such as propranolol and metoprolol. The peripheral vasoconstriction caused by high doses of dopamine HCl is antagonized by α-adrenergic blocking agents. Dopamine-induced renal and mesenteric vasodilation is not antagonized by either α- or β-adrenergic blocking agents.

Butyrophenones (such as haloperidol) and phenothiazines can suppress the dopaminergic renal and mesenteric vasodilation induced with low-dose dopamine infusion.

The concomitant use of vasopressors, vasoconstricting agents (such as ergonovine) and some oxytocic drugs may result in severe hypertension.

Administration of phenytoin to patients receiving dopamine HCl has been reported to lead to hypotension and bradycardia. It is suggested that in patients receiving dopamine HCl, alternatives to phenytoin should be considered if anticonvulsant therapy is needed.

Carcinogenesis, Mutagenesis, Impairment of Fertility: Long term animal studies have not been performed to evaluate the carcinogenic potential of dopamine HCl.

Dopamine HCl at doses approaching maximal solubility showed no clear genotoxic potential in the Ames test. Although there was a reproducible dose-dependent increase in the number of revertant colonies with strains TA100 and TA98, both with and without metabolic activation, the small increase was considered inconclusive evidence of mutagenicity. In the L5178Y TK+/- mouse lymphoma assay, dopamine HCl at the highest concentrations used of 750 μg/mL without metabolic activation, and 3000 μg/mL with activation, was toxic and associated with increases in mutant frequencies when compared to untreated and solvent controls; at the lower concentrations no increases over controls were noted.

No clear evidence of clastogenic potential was reported in the in vivo mouse or male rat bone marrow micronucleus test when the animals were treated intravenously with up to 224 mg/kg and 30 mg/kg of dopamine HCl, respectively.

Pregnancy: Teratogenic Effects: Teratogenicity studies in rats and rabbits at dopamine HCl dosages up to 6 mg/kg/day intravenously during organogenesis produced no detectable teratogenic or embryotoxic effects, although maternal toxicity consisting of mortalities, decreased body weight gain, and pharmacotoxic signs were observed in rats. In a published study, dopamine HCl administered at 10 mg/kg subcutaneously for 30 days, markedly prolonged metestrus and increased mean pituitary and ovary weights in female rats. Similar administration to pregnant rats throughout gestation or for 5 days starting on gestation day 10 or 15 resulted in decreased body weight gains, increased mortalities and slight increases in cataract formation among the offspring. There are no adequate and well-controlled studies in pregnant women, and it is not known if dopamine HCl crosses the placental barrier. Dopamine HCl should be used during pregnancy only if the potential benefit justifies the potential risk to the fetus.

Labor and Delivery: In obstetrics, if vasopressor drugs are used to correct hypotension or are added to a local anesthetic solution the interaction with some oxytocic drugs may cause severe hypertension.

Nursing Mothers: It is not known whether this drug is excreted in human milk. Because many drugs are excreted in human milk, caution should be exercised when dopamine HCl is administered to a nursing mother.

Pediatric Use: Dopamine infusions have been used in patients of every age from birth onwards. There are scattered reports of infusion rates in neonates up to 125 mcg/kg/min, but most reports in pediatric patients describe dosing that is similar (on a mcg/kg/min basis) to that used in adults. Except for vasoconstrictive effects caused by inadvertent infusion of dopamine into the umbilical artery, adverse effects unique to the pediatric population have not been identified, nor have adverse effects identified in adults been found to be more common in pediatric patients.

Geriatric Use: Clinical studies of dopamine injection did not include sufficient numbers of subjects aged 65 and over to determine whether they respond differently from younger subjects. Other reported clinical experience has not identified differences in responses between the elderly and younger patients. In general, dose selection for an elderly patient should be cautious, usually starting at the low end of the dosing range, reflecting the frequency of decreased hepatic, renal or cardiac function, and of concomitant disease or other drug therapy.

ADVERSE REACTIONS

The following adverse reactions have been observed, but there are not enough data to support an estimate of their frequency.

Cardiovascular System
ventricular arrhythmia
atrial fibrillation
ectopic beats
tachycardia
anginal pain
palpitation
cardiac conduction abnormalities
widened QRS complex
bradycardia
hypotension
hypertension
vasoconstriction

Respiratory System
dyspnea

Gastrointestinal System
nausea
vomiting

Metabolic/Nutritional System
azotemia

Central Nervous System
headache
anxiety

Dermatological System
piloerection

Other
Gangrene of the extremities has occurred when high doses were administered for prolonged periods or in patients with occlusive vascular disease receiving low doses of dopamine HCl.

OVERDOSAGE

In the case of accidental overdosage, as evidenced by excessive blood pressure elevation, reduce rate of infusion, or temporarily discontinue administration of the drug until patient's condition stabilizes. Since dopamine's duration of action is quite short, no additional remedial measures are usually necessary. If these measures fail to stabilize the patient's condition, consider using an alpha-adrenergic blocking agent (e.g., phentolamine).

DOSAGE & ADMINISTRATION

Do NOT administer if solution is darker than slightly yellow or discolored in any other way. Do NOT administer unless solution is clear and container is undamaged. Discard unused portion.

Dextrose solutions without electrolytes should not be administered simultaneously with blood through the same infusion set because of the possibility that pseudoagglutination of red cells may occur.

Do NOT add sodium bicarbonate or other alkalinizing substance, since dopamine is inactivated in alkaline solution.

Dopamine Hydrochloride in 5% Dextrose Injection should be infused into a large vein whenever possible to prevent the infiltration of perivascular tissue adjacent to the infusion site. Extravasation may cause necrosis and sloughing of the surrounding tissue. Large veins of the antecubital fossa are preferred to veins of the dorsum of the hand or ankle. Less suitable infusion sites should be used only when larger veins are unavailable and the patient's condition requires immediate attention. The physician should switch to a more suitable site as soon as possible and the infusion site in use should be continuously monitored for free flow.

The less concentrated 800 mcg/mL solution may be preferred when fluid expansion is not a problem. The more concentrated 1600 mcg/mL or 3200 mcg/mL solutions, may be preferred in patients with fluid retention or when a slower rate of infusion is desired.

Rate of Administration: Administration into an umbilical artery catheter is not recommended.

Dopamine in 5% Dextrose Injection should not be infused through ordinary intravenous apparatus, regulated only by gravity and mechanical clamps. Only an infusion pump, preferably a volumetric pump, should be used.

Each patient must be individually titrated to the desired hemodynamic or renal response to dopamine.

In titrating to the desired increase in systolic blood pressure, the optimum dosage rate for renal response may be exceeded, thus necessitating a reduction in rate after the hemodynamic condition is stabilized.

If a disproportionate rise in diastolic pressure (i.e., a marked decrease in pulse pressure) is observed in patients receiving dopamine, the infusion rate should be decreased and the patient observed carefully for further evidence of predominant vasoconstrictor activity, unless such an effect is desired.

Administration rates greater than 50 mcg/kg/min have safely been used in adults in advanced circulatory decompensation states. If unnecessary fluid expansion is of concern, adjustment of drug concentration may be preferred over increasing the flow rate of a less concentrated dilution.

When discontinuing the infusion, it may be necessary to gradually decrease the dose of dopamine HCl while expanding the blood volume with intravenous fluids to prevent the development of marked hypotension.

Suggested Regimen:

1.
When appropriate, increase blood volume with whole blood or plasma until central venous pressure is 10 to 15 cm H 2O or pulmonary wedge pressure is 14 to 18 mm Hg.
2.
Begin infusion of dopamine hydrochloride solution at doses of 2 to 5 mcg/kg/min in adult or pediatric patients who are likely to respond to modest increments of heart force and renal perfusion.
In more seriously ill patients, begin infusion of dopamine hydrochloride at doses of 5 mcg/kg/min and increase gradually, using 5 to 10 mcg/kg/min increments, up to a rate of 20 to 50 mcg/kg/min as needed. If doses in excess of 50 mcg/kg/min are required, check urine output frequently. Should urinary flow begin to decrease in the absence of hypotension, reduction of dopamine dosage should be considered. More than 50% of adult patients have been satisfactorily maintained on doses less than 20 mcg/kg/min.
In patients who do not respond to these doses with adequate arterial pressures or urine flow, additional increments of dopamine may be given in an effort to produce an appropriate arterial pressure and central perfusion.
3.
Treatment of all patients requires constant evaluation of therapy in terms of blood volume, augmentation of cardiac contractility, urine flow, cardiac output, blood pressure, and distribution of peripheral perfusion.
Dosage of dopamine should be adjusted according to the patient's response. Diminution of established urine flow rate, increasing tachycardia or development of new dysrhythmias are reasons to consider decreasing or temporarily suspending the dosage.
4.
As with all potent intravenously administered drugs, care should be taken to control the rate of infusion so as to avoid inadvertent administration of a bolus of the drug.

800 mcg/mL Dosing Chart for Dopamine (mL/hr) Infusion Rate

1600 mcg/mL Dosing Chart for Dopamine (mL/hr) Infusion Rate

3200 mcg/mL Dosing Chart for Dopamine (mL/hr) Infusion Rate

Parenteral drug products should be visually inspected for particulate matter and discoloration prior to administration, whenever solution and container permit.

INSTRUCTIONS FOR USE

To Open

Tear outer wrap at notch and remove solution container. Some opacity of the plastic due to moisture absorption during the sterilization process may be observed. This is normal and does not affect the solution quality or safety. The opacity will diminish gradually.

Preparation for Administration
(Use aseptic technique)

1.
Close flow control clamp of administration set.
2.
Remove cover from outlet port at bottom of container.
3.
Insert piercing pin of administration set into port with a twisting motion until the set is firmly seated. NOTE: See full directions on administration set carton.
4.
Suspend container from hanger.
5.
Squeeze and release drip chamber to establish proper fluid level in chamber.
6.
Open flow control clamp and clear air from set. Close clamp.
7.
Attach set to venipuncture device. If device is not indwelling, prime and make venipuncture.
8.
Regulate rate of administration with an infusion pump, preferably a volumetric pump.

WARNING: Do not use flexible container in series connections.

HOW SUPPLIED

DOPAMINE HYDROCHLORIDE IN 5% DEXTROSE INJECTION, USP is supplied in the following dosage forms.
NDC 51662-1316-1
DOPAMINE HYDROCHLORIDE IN 5% DEXTROSE INJECTION, USP 400mg 250mL BAG

NDC 51662-1316-2
DOPAMINE HYDROCHLORIDE IN 5% DEXTROSE INJECTION, USP 400mg 250mL BAG, 1 BAG IN A POUCH

NDC 51662-1316-3
DOPAMINE HYDROCHLORIDE IN 5% DEXTROSE INJECTION, USP 400mg 250mL BAG, IN A POUCH, 12 POUCHES PER CASE

HF Acquisition Co LLC, DBA HealthFirst
Mukilteo, WA 98275

Also supplied in the following manufacture supplied dosage forms

Dopamine Hydrochloride in 5% Dextrose Injection, USP is supplied in 250 and 500 mL LifeCare flexible containers as follows:

Avoid contact with alkalies (including sodium bicarbonate), oxidizing agents or iron salts.

Do not use the injection if it is darker than slightly yellow or discolored in any other way.

Store at 20 to 25°C (68 to 77°F). [See USP Controlled Room Temperature.] Protect from freezing.

Distributed by Hospira, Inc., Lake Forest, IL 60045 USA

LAB-1153-1.0

Revised: 03/2018

PRINCIPAL DISPLAY PANEL NDC 51662-1316-2 POUCH LABELING

BAG LABELING

PRINCIPAL DISPLAY PANEL NDC 51662-1316-2 POUCH LABELING

BAG LABELING

BAG 2

51662-1316-2 POUCH LABELING

PRINCIPAL DISPLAY PANEL NDC 51662-1316-3 CASE LABELING

NDC 51662-1316-3 CASE LABELING

SERIALIZED RFID